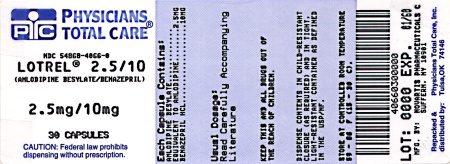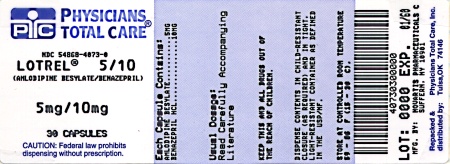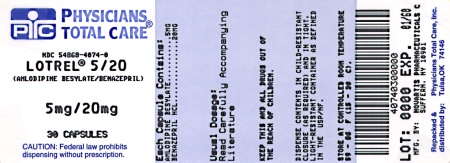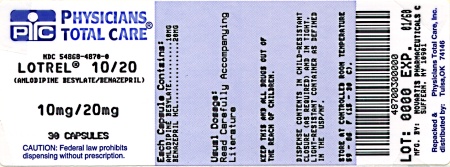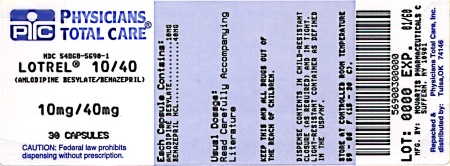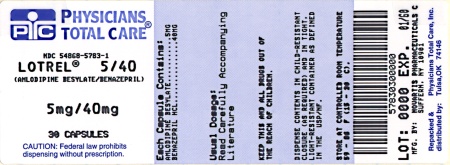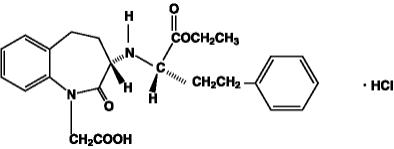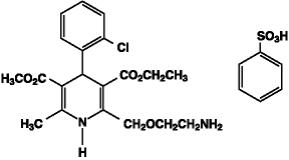 DRUG LABEL: Lotrel
NDC: 54868-4066 | Form: CAPSULE
Manufacturer: Physicians Total Care, Inc.
Category: prescription | Type: HUMAN PRESCRIPTION DRUG LABEL
Date: 20120302

ACTIVE INGREDIENTS: AMLODIPINE BESYLATE 2.5 mg/1 1; BENAZEPRIL HYDROCHLORIDE 10 mg/1 1
INACTIVE INGREDIENTS: CALCIUM PHOSPHATE; HYPROMELLOSES; SILICON DIOXIDE; CROSPOVIDONE; GELATIN; HYDROGENATED CASTOR OIL; FERRIC OXIDE RED; LACTOSE; MAGNESIUM STEARATE; POLYSORBATE 80; SILICON DIOXIDE; SODIUM LAURYL SULFATE; SODIUM STARCH GLYCOLATE TYPE A POTATO; STARCH, CORN; TALC; TITANIUM DIOXIDE

HIGHLIGHTS OF PRESCRIBING INFORMATION

These highlights do not include all the information needed to use Lotrel safely and effectively. See full prescribing information for Lotrel.
Lotrel (amlodipine besylate and benazepril hydrochloride) Capsules
Initial U.S. Approval: 1995

RECENT MAJOR CHANGES

Boxed Warning: Fetal Toxicity 01/2012

Warnings and Precautions: Fetal Toxicity (5.4) 01/2012

WARNING: FETAL TOXICITY

See full prescribing information for complete boxed warning

When pregnancy is detected, discontinue Lotrel as soon as possible (5.4). Drugs that act directly on the renin-angiotensin system can cause injury and death to the developing fetus (5.4).

1 INDICATIONS AND USAGE

Lotrel is a combination tablet of amlodipine, a dihydropyridine calcium channel blocker (DHP CCB) and benazepril, an angiotensin converting enzyme (ACE) inhibitor. Lotrel is indicated for the treatment of hypertension in patients not adequately controlled on monotherapy with either agent (1)

2 DOSAGE AND ADMINISTRATION

- Dose once-daily
- May be used as add-on therapy for patients not adequately controlled with either a dihydropyridine calcium channel blocker or an ACE inhibitor (2.2)
- Patients who experience edema with amlodipine may be switched to Lotrel containing a lower dose of amlodipine (2.2)
- Start Lotrel at 2.5/10 mg in patients ≥ 75 years old or in patients with hepatic impairment (2)

3 DOSAGE FORMS AND STRENGTHS

Capsules (amlodipine/benazepril mg): 2.5/10, 5/10, 5/20, 5/40, 10/20, 10/40 (3)

4 CONTRAINDICATIONS

Lotrel is contraindicated in patients with a history of angioedema, with or without previous ACE inhibitor treatment, or patients who are hypersensitive to benazepril, to any other ACE inhibitor, or to amlodipine. (4)

5 WARNINGS AND PRECAUTIONS

- Watch for anaphylactoid reactions, including angioedema (head, neck or intestinal).
- Warn patients with severe obstructive coronary artery disease about the risk of myocardial infarction or increased angina (5.2)
- Assess for hypotension and hyperkalemia (5.3 and 5.7)
- Titrate slowly in patients with impaired hepatic (5.5) or severely impaired renal (5.6) function.

6 ADVERSE REACTIONS

Discontinuation because of adverse reactions occurred in 4% of Lotrel-treated patients and 3% of placebo-treated patients. The most common reasons for discontinuation of therapy with Lotrel were cough and edema. (6)

To report SUSPECTED ADVERSE REACTIONS, contact Novartis Pharmaceuticals Corporation at 1-888-669-6682 or FDA at 1-800-FDA-1088 or www.fda.gov/medwatch.

7 DRUG INTERACTIONS

- Potassium supplements / Potassium-sparing diuretics: risk of hyperkalemia
- Lithium: Increased serum Lithium levels; toxicity symptoms
- Injectable gold: facial flushing, nausea, vomiting, or hypotension may occur
- NSAID: Risk of renal dysfunction, loss of antihypertensive effect (7.1)
- If simvastatin is co-administered with amlodipine, do not exceed doses greater than 20 mg daily of simvastatin (7.1)

8 USE IN SPECIFIC POPULATIONS

Nursing Mothers: It is not known whether amlodipine is excreted in human milk. Nursing or drug should be discontinued. (8.3)

FULL PRESCRIBING INFORMATION

WARNING: FETAL TOXICITY

When pregnancy is detected, discontinue Lotrel as soon as possible (5.4). Drugs that act directly on the renin-angiotensin system can cause injury and death to the developing fetus (5.4)

1 INDICATIONS AND USAGE

1.1 Hypertension

Lotrel is indicated for the treatment of hypertension in patients not adequately controlled on monotherapy with either agent.

2 DOSAGE AND ADMINISTRATION

Amlodipine is an effective treatment of hypertension in once-daily doses of 2.5-10 mg while benazepril is effective in doses of 10-80 mg. In clinical trials of amlodipine/benazepril combination therapy using amlodipine doses of 2.5-10 mg and benazepril doses of 10-40 mg, the antihypertensive effects increased with increasing dose of amlodipine in all patient groups, and the effects increased with increasing dose of benazepril in nonblack groups.

The antihypertensive effect of Lotrel is largely attained within 2 weeks.

It is usually appropriate to begin therapy with Lotrel only after a patient has either (a) failed to achieve the desired antihypertensive effect with one or the other monotherapy, or (b) demonstrated inability to achieve adequate antihypertensive effect with amlodipine therapy without developing edema.

Renal Impairment: Regimens of therapy with Lotrel need not take account of renal function as long as the patient’s creatinine clearance is >30 mL/min/1.73m^2 (serum creatinine roughly ≤3 mg/dL or 265 µmol/L). Lotrel is not recommended in patients with more severe renal impairment.

Hepatic Impairment and Elderly Patients: The recommended initial dose of amlodipine, as monotherapy or as a component of combination therapy, is 2.5 mg.

2.2 Add-on Therapy

A patient whose blood pressure is not adequately controlled with amlodipine (or another dihydropyridine) alone or with benazepril (or another ACE inhibitor) alone may be switched to combination therapy with Lotrel.

In patients whose blood pressure is adequately controlled with amlodipine but who experience unacceptable edema, combination therapy may achieve similar (or better) blood pressure control with less edema.

2.3 Replacement Therapy

Lotrel may be substituted for the titrated components.

3 DOSAGE FORMS AND STRENGTHS

Lotrel (amlodipine/benazepril) capsules are available as follows:

2.5/10 mg, 5/10 mg, 5/20 mg, 5/40 mg, 10/20 mg, and 10/40 mg.

4 CONTRAINDICATIONS

Lotrel is contraindicated in patients with a history of angioedema, with or without previous ACE inhibitor treatment, or patients who are hypersensitive to benazepril, to any other ACE inhibitor, or to amlodipine.

5 WARNINGS AND PRECAUTIONS

5.1 Anaphylactoid and Possibly Related Reactions

Presumably because angiotensin-converting enzyme inhibitors affect the metabolism of eicosanoids and polypeptides, including endogenous bradykinin, patients receiving ACE inhibitors (including Lotrel) may be subject to a variety of adverse reactions, some of them serious. These reactions usually occur after one of the first few doses of the ACE inhibitor, but they sometimes do not appear until after months of therapy. Black patients receiving ACE inhibitors have a higher incidence of angioedema compared to nonblacks.

Head and Neck Angioedema: Angioedema of the face, extremities, lips, tongue, glottis, and larynx has been reported in patients treated with ACE inhibitors. In U.S. clinical trials, symptoms consistent with angioedema were seen in none of the subjects who received placebo and in about 0.5% of the subjects who received benazepril. Angioedema associated with laryngeal edema can be fatal. If laryngeal stridor or angioedema of the face, tongue, or glottis occurs, discontinue treatment with Lotrel and treat immediately. When involvement of the tongue, glottis, or larynx appears likely to cause airway obstruction, appropriate therapy, e.g., administer subcutaneous epinephrine injection 1:1000 (0.3-0.5 mL), promptly [see Adverse Reactions (6)].

Intestinal Angioedema: Intestinal angioedema has been reported in patients treated with ACE inhibitors. These patients presented with abdominal pain (with or without nausea or vomiting); in some cases there was no prior history of facial angioedema and C-1 esterase levels were normal. The angioedema was diagnosed by procedures including abdominal CT scan or ultrasound, or at surgery, and symptoms resolved after stopping the ACE inhibitor. Intestinal angioedema should be included in the differential diagnosis of patients on ACE inhibitors presenting with abdominal pain.

Anaphylactoid Reactions During Desensitization: Two patients undergoing desensitizing treatment with hymenoptera venom while receiving ACE inhibitors sustained life-threatening anaphylactoid reactions. In the same patients, these reactions were avoided when ACE inhibitors were temporarily withheld, but they reappeared upon inadvertent rechallenge.

Anaphylactoid Reactions During Membrane Exposure: Anaphylactoid reactions have been reported in patients dialyzed with high-flux membranes and treated concomitantly with an ACE inhibitor. Anaphylactoid reactions have also been reported in patients undergoing low-density lipoprotein apheresis with dextran sulfate absorption.

5.2 Increased Angina and/or Myocardial Infarction

Rarely, patients, particularly those with severe obstructive coronary artery disease, have developed documented increased frequency, duration or severity of angina or acute myocardial infarction on starting calcium channel blocker therapy or at the time of dosage increase. The mechanism of this effect has not been elucidated.

5.3 Hypotension

Lotrel can cause symptomatic hypotension. Symptomatic hypotension is most likely to occur in patients who have been volume or salt depleted as a result of prolonged diuretic therapy, dietary salt restriction, dialysis, diarrhea, or vomiting.

In patients with congestive heart failure, with or without associated renal insufficiency, ACE inhibitor therapy may cause excessive hypotension, which may be associated with oliguria, azotemia, and (rarely) with acute renal failure and death. In such patients, start Lotrel therapy under close medical supervision; follow closely for the first 2 weeks of treatment and whenever the dose of the benazepril component is increased or a diuretic is added or its dose increased.

Symptomatic hypotension is also possible in patients with severe aortic stenosis.

If hypotension occurs, place the patient in a supine position, and if necessary, treat with intravenous infusion of physiologic saline. Lotrel treatment usually can be continued following restoration of blood pressure and volume.

5.4 Fetal Toxicity

Pregnancy Category D

Use of drugs that act on the renin-angiotensin system during the second and third trimesters of pregnancy reduces fetal renal function and increases fetal and neonatal morbidity and death. Resulting oligohydramnios can be associated with fetal lung hypoplasia and skeletal deformations. Potential neonatal adverse effects include skull hypoplasia, anuria, hypotension, renal failure, and death. When pregnancy is detected, discontinue Lotrel as soon as possible [see Use in Specific Populations (8.1)].

5.5 Hepatic Failure

Rarely, ACE inhibitors have been associated with a syndrome that starts with cholestatic jaundice and progresses to fulminant hepatic necrosis and, sometimes, death. The mechanism of this syndrome is not understood. Patients receiving ACE inhibitors who develop jaundice or marked elevations of hepatic enzymes should discontinue the ACE inhibitor and receive appropriate medical follow-up.

In patients with hepatic dysfunction due to cirrhosis, levels of benazeprilat are essentially unaltered.

However, since amlodipine is extensively metabolized by the liver and the plasma elimination half-life (t1/2) is 56 hours in patients with impaired hepatic function, titrate Lotrel slowly in patients with severe hepatic impairment.

5.6 Impaired Renal Function

Lotrel should not be used in patients with severe renal disease (Clearance creatinine < 30 ml/min) [see Dosage and Administration (2)].

In patients with severe heart failure, whose renal function may depend on the activity of the renin-angiotensin aldosterone system, treatment with benazepril may be associated with oliguria or progressive azotemia and (rarely) with acute renal failure and/or death.

In a small study of hypertensive patients with unilateral or bilateral renal artery stenosis, treatment with benazepril was associated with increases in blood urea nitrogen and serum creatinine; these increases were reversible upon discontinuation of benazepril therapy, concomitant diuretic therapy, or both. When such patients are treated with Lotrel, monitor renal function during the first few weeks of therapy.

Some benazepril-treated hypertensive patients with no apparent preexisting renal vascular disease have developed increases in blood urea nitrogen and serum creatinine, usually minor and transient, especially when benazepril has been given concomitantly with a diuretic. Dosage reduction of Lotrel may be required.

Renal function should be monitored periodically in patients receiving benazepril.

5.7 Hyperkalemia

In U.S. placebo-controlled trials of Lotrel, hyperkalemia (serum potassium at least 0.5 mEq/L greater than the upper limit of normal) not present at baseline occurred in approximately 1.5% of hypertensive patients receiving Lotrel. Increases in serum potassium were generally reversible. Risk factors for the development of hyperkalemia include renal insufficiency, diabetes mellitus, and the concomitant use of potassium-sparing diuretics, potassium supplements, and/or potassium-containing salt substitutes. Serum potassium should be monitored periodically in patients receiving benazepril.

5.8 Cough

Presumably due to the inhibition of the degradation of endogenous bradykinin, persistent nonproductive cough has been reported with all ACE inhibitors, generally resolving after discontinuation of therapy. Consider ACE inhibitor-induced cough in the differential diagnosis of cough.

5.9 Surgery/Anesthesia

In patients undergoing surgery or during anesthesia with agents that produce hypotension, benazepril will block the angiotensin II formation that could otherwise occur secondary to compensatory renin release. Hypotension that occurs as a result of this mechanism can be corrected by volume expansion.

6 ADVERSE REACTIONS

6.1 Clinical Trials Experience

Because clinical trials are conducted under widely varying conditions, adverse reaction rates observed in the clinical trials of a drug cannot be directly compared to rates in the clinical trials of another drug and may not reflect the rates observed in practice. The adverse reaction information from clinical trials does, however, provide a basis for identifying the adverse events that appear to be related to drug use and for approximating rates.

Lotrel has been evaluated for safety in over 2,991 patients with hypertension; over 500 of these patients were treated for at least 6 months, and over 400 were treated for more than 1 year.

In a pooled analysis of 5 placebo-controlled trials involving Lotrel doses up to 5/20, the reported side effects were generally mild and transient, and there was no relationship between side effects and age, sex, race, or duration of therapy. Discontinuation of therapy due to side effects was required in approximately 4% of patients treated with Lotrel and in 3% of patients treated with placebo.

The most common reasons for discontinuation of therapy with Lotrel in these studies were cough and edema (including angioedema).

The peripheral edema associated with amlodipine use is dose-dependent. When benazepril is added to a regimen of amlodipine, the incidence of edema is substantially reduced.

The addition of benazepril to a regimen of amlodipine should not be expected to provide additional antihypertensive effect in African-Americans. However, all patient groups benefit from the reduction in amlodipine-induced edema.

The side effects considered possibly or probably related to study drug that occurred in these trials in more than 1% of patients treated with Lotrel are shown in the table below. Cough was the only adverse event with at least possible relationship to treatment that was more common on Lotrel (3.3%) than on placebo (0.2%).

PERCENT INCIDENCE IN U.S. PLACEBO-CONTROLLED TRIALS
 | Benazepril/Amlodipine | Benazepril | Amlodipine | Placebo
 | N=760 | N=554 | N=475 | N=408
Cough | 3.3 | 1.8 | 0.4 | 0.2
Headache | 2.2 | 3.8 | 2.9 | 5.6
Dizziness | 1.3 | 1.6 | 2.3 | 1.5
Edema* | 2.1 | 0.9 | 5.1 | 2.2

*Edema refers to all edema, such as dependent edema, angioedema, facial edema.

The incidence of edema was greater in patients treated with amlodipine monotherapy (5.1%) than in patients treated with Lotrel (2.1%) or placebo (2.2%).

Other side effects considered possibly or probably related to study drug that occurred in U.S. placebo-controlled trials of patients treated with Lotrel or in postmarketing experience were the following:

Body as a Whole: Asthenia and fatigue.

CNS: Insomnia, nervousness, anxiety, tremor, and decreased libido.

Dermatologic: Flushing, hot flashes, rash, skin nodule, and dermatitis.

Digestive: Dry mouth, nausea, abdominal pain, constipation, diarrhea, dyspepsia, and esophagitis.

Hematologic: Neutropenia

Metabolic and Nutritional: Hypokalemia.

Musculoskeletal: Back pain, musculoskeletal pain, cramps, and muscle cramps.

Respiratory: Pharyngitis.

Urogenital: Sexual problems such as impotence, and polyuria.

Monotherapies of benazepril and amlodipine have been evaluated for safety in clinical trials in over 6,000 and 11,000 patients, respectively. The observed adverse reactions to the monotherapies in these trials were similar to those seen in trials of Lotrel.

6.2 Post-marketing Experience

Because these reactions are reported voluntarily from a population of uncertain size, it is not always possible to reliably estimate their frequency or establish a causal relationship to drug exposure.

In postmarketing experience with benazepril, there have been rare reports of Stevens-Johnson syndrome, pancreatitis, hemolytic anemia, pemphigus, and thrombocytopenia. Gingival hyperplasia, tachycardia, jaundice, and hepatic enzyme elevations (mostly consistent with cholestasis severe enough to require hospitalization) have been reported in association with use of amlodipine. Other potentially important adverse experiences attributed to other ACE inhibitors and calcium channel blockers include: eosinophilic pneumonitis (ACE inhibitors) and gynecomastia (CCBs). Other infrequently reported events included chest pain, ventricular extrasystole, gout, neuritis, tinnitus, alopecia, upper respiratory tract infection, palpitations and somnolence.

7 DRUG INTERACTIONS

7.1 Drug/Drug interactions

Diuretics: Patients on diuretics, especially those in whom diuretic therapy was recently instituted, may occasionally experience an excessive reduction of blood pressure after initiation of therapy with Lotrel. The possibility of hypotensive effects with Lotrel can be minimized by either discontinuing the diuretic or increasing the salt intake prior to initiation of treatment with Lotrel.

Potassium Supplements and Potassium-Sparing Diuretics: Benazepril can attenuate potassium loss caused by thiazide diuretics. Potassium-sparing diuretics (spironolactone, amiloride, triamterene, and others) or potassium supplements can increase the risk of hyperkalemia. If concomitant use of such agents is indicated, the patient’s serum potassium should be monitored frequently.

Lithium: Increased serum lithium levels and symptoms of lithium toxicity have been reported in patients receiving ACE inhibitors during therapy with lithium. When coadministering Lotrel and lithium, frequent monitoring of serum lithium levels is recommended.

Gold: Nitritoid reactions (symptoms include facial flushing, nausea, vomiting and hypotension) have been reported rarely in patients on therapy with injectable gold (sodium aurothiomalate) and concomitant ACE inhibitor therapy.

Non-Steroidal Anti-Inflammatory Agents including Selective Cyclooxygenase-2 Inhibitors (COX-2 Inhibitors): In patients who are elderly, volume-depleted (including those on diuretic therapy), or with compromised renal function, co-administration of NSAIDs, including selective COX-2 inhibitors, with ACE inhibitors, including benazepril, may result in deterioration of renal function, including possible acute renal failure. These effects are usually reversible. Monitor renal function periodically in patients receiving benazepril and NSAID therapy.

The antihypertensive effect of ACE inhibitors, including benazepril, may be attenuated by NSAIDs.

Simvastatin: Co-administration of multiple doses of 10 mg of amlodipine with 80 mg simvastatin resulted in a 77% increase in exposure to simvastatin compared to simvastatin alone. Limit the dose of simvastatin in patients on amlodipine to 20 mg daily.

Other: Benazepril has been used concomitantly with oral anticoagulants, beta-adrenergic-blocking agents, calcium-blocking agents, cimetidine, diuretics, digoxin, and hydralazine without evidence of clinically important adverse interactions.

In clinical trials, amlodipine has been safely administered with thiazide diuretics, beta-blockers, ACE inhibitors, long-acting nitrates, sublingual nitroglycerin, digoxin, warfarin, nonsteroidal anti-inflammatory drugs, antibiotics, and oral hypoglycemic drugs.

In vitro data in human plasma indicate that amlodipine has no effect on the protein binding of drugs tested (digoxin, phenytoin, warfarin, and indomethacin). Special studies have indicated that the coadministration of amlodipine with digoxin did not change serum digoxin levels or digoxin renal clearance in normal volunteers; that coadministration with cimetidine did not alter the pharmacokinetics of amlodipine; and that coadministration with warfarin did not change the warfarin-induced prothrombin response time.

7.2 Clinical Laboratory Test Findings

Serum Electrolytes: [see Warnings and Precautions (5)].

Creatinine: Minor reversible increases in serum creatinine were observed in patients with essential hypertension treated with Lotrel. Increases in creatinine are more likely to occur in patients with renal insufficiency or those pretreated with a diuretic and, based on experience with other ACE inhibitors, would be expected to be especially likely in patients with renal artery stenosis [see Warnings and Precautions (5)].

Other (causal relationships unknown): Clinically important changes in standard laboratory tests were rarely associated with Lotrel administration. Elevations of serum bilirubin and uric acid have been reported as have scattered incidents of elevations of liver enzymes.

8 USE IN SPECIFIC POPULATIONS

8.1 Pregnancy

Pregnancy Category D

Use of drugs that act on the renin-angiotensin system during the second and third trimesters of pregnancy reduces fetal renal function and increases fetal and neonatal morbidity and death. Resulting oligohydramnios can be associated with fetal lung hypoplasia and skeletal deformations. Potential neonatal adverse effects include skull hypoplasia, anuria, hypotension, renal failure, and death. When pregnancy is detected, discontinue Lotrel as soon as possible. These adverse outcomes are usually associated with use of these drugs in the second and third trimester of pregnancy. Most epidemiologic studies examining fetal abnormalities after exposure to antihypertensive use in the first trimester have not distinguished drugs affecting the renin-angiotensin system from other antihypertensive agents. Appropriate management of maternal hypertension during pregnancy is important to optimize outcomes for both mother and fetus.

In the unusual case that there is no appropriate alternative to therapy with drugs affecting the renin-angiotensin system for a particular patient, apprise the mother of the potential risk to the fetus. Perform serial ultrasound examinations to assess the intra-amniotic environment. If oligohydramnios is observed, discontinue Lotrel, unless it is considered lifesaving for the mother. Fetal testing may be appropriate, based on the week of pregnancy. Patients and physicians should be aware, however, that oligohydramnios may not appear until after the fetus has sustained irreversible injury. Closely observe infants with histories of in utero exposure to Lotrel for hypotension, oliguria, and hyperkalemia [see Use in Specific Populations (8.4)].

8.2 Labor and Delivery

The effect of Lotrel on labor and delivery has not been studied.

8.3 Nursing Mothers

Minimal amounts of unchanged benazepril and of benazeprilat are excreted into the breast milk of lactating women treated with benazepril, so that a newborn child ingesting nothing but breast milk would receive less than 0.1% of the maternal doses of benazepril and benazeprilat.

It is not known whether amlodipine is excreted in human milk. Nursing or drug should be discontinued.

8.4 Pediatric Use

Neonates with a history of in utero exposure to Lotrel:

If oliguria or hypotension occurs, direct attention toward support of blood pressure and renal perfusion. Exchange transfusions or dialysis may be required as a means of reversing hypotension and/or substituting for disordered renal function. Benazepril, which crosses the placenta, can theoretically be removed from the neonatal circulation by these means; there are occasional reports of benefit from these maneuvers, but experience is limited.

8.5 Geriatric Use

Of the total number of patients who received Lotrel in U.S. clinical studies of Lotrel, over 19% were 65 or older while about 2% were 75 or older. Overall differences in effectiveness or safety were not observed between these patients and younger patients. Clinical experience has not identified differences in responses between the elderly and younger patients, but greater sensitivity of some older individuals cannot be ruled out.

Benazepril and benazeprilat are substantially excreted by the kidney. Because elderly patients are more likely to have decreased renal function, care should be taken in dose selection, and it may be useful to monitor renal function.

Amlodipine is extensively metabolized in the liver. In the elderly, clearance of amlodipine is decreased with resulting increases in peak plasma levels, elimination half-life and area-under-the-plasma-concentration curve. Thus a lower starting dose may be required in older patients [see Dosage and Administration (2)].

10 OVERDOSAGE

Only a few cases of human overdose with amlodipine have been reported. One patient was asymptomatic after a 250-mg ingestion; another, who combined 70 mg of amlodipine with an unknown large quantity of a benzodiazepine, developed refractory shock and died.

Human overdoses with any combination of amlodipine and benazepril have not been reported. In scattered reports of human overdoses with benazepril and other ACE inhibitors, there are no reports of death.

Treatment: To obtain up-to-date information about the treatment of overdose, a good resource is your certified Regional Poison-Control Center. Telephone numbers of certified poison-control centers are listed in the Physicians’ Desk Reference (PDR). In managing overdose, consider the possibilities of multiple-drug overdoses, drug-drug interactions, and unusual drug kinetics in your patient.

The most likely effect of overdose with Lotrel is vasodilation, with consequent hypotension and tachycardia. Simple repletion of central fluid volume (Trendelenburg positioning, infusion of crystalloids) may be sufficient therapy, but pressor agents (norepinephrine or high-dose dopamine) may be required. With abrupt return of peripheral vascular tone, overdoses of other dihydropyridine calcium channel blockers have sometimes progressed to pulmonary edema, and patients must be monitored for this complication.

Analyses of bodily fluids for concentrations of amlodipine, benazepril, or their metabolites are not widely available. Such analyses are, in any event, not known to be of value in therapy or prognosis.

No data are available to suggest physiologic maneuvers (e.g., maneuvers to change the pH of the urine) that might accelerate elimination of amlodipine, benazepril, or their metabolites. Benazeprilat is only slightly dialyzable; attempted clearance of amlodipine by hemodialysis or hemo-perfusion has not been reported, but amlodipine’s high protein binding makes it unlikely that these interventions will be of value.

Angiotensin II could presumably serve as a specific antagonist-antidote to benazepril, but angiotensin II is essentially unavailable outside of scattered research laboratories.

11 DESCRIPTION

Lotrel is a combination of amlodipine besylate and benazepril hydrochloride.

Benazepril hydrochloride is a white to off-white crystalline powder, soluble (>100 mg/mL) in water, in ethanol, and in methanol. Benazepril hydrochloride’s chemical name is 3-[[1-(ethoxycarbonyl)-3-phenyl-(1S)-propyl]amino]-2,3,4,5-tetrahydro-2-oxo-1H-1-(3S)-benzazepine-1-acetic acid monohydrochloride; its structural formula is

Its empirical formula is C24H28N2O5•HCl, and its molecular weight is 460.96.

Benazeprilat, the active metabolite of benazepril, is a nonsulfhydryl angiotensin-converting enzyme (ACE) inhibitor. Benazepril is converted to benazeprilat by hepatic cleavage of the ester group.

Amlodipine besylate is a white to pale yellow crystalline powder, slightly soluble in water and sparingly soluble in ethanol. Its chemical name is (R,S)3-ethyl-5-methyl-2-(2-aminoethoxymethyl)-4-(2-chlorophenyl)-1,4-dihydro-6-methyl-3,5-pyridinedicarboxylate benzenesulfonate; its structural formula is

Its empirical formula is C20H25ClN2O5•C6H6O3S, and its molecular weight is 567.1.

Amlodipine besylate is the besylate salt of amlodipine, a dihydropyridine calcium channel blocker.

Lotrel capsules are formulated in six different strengths for oral administration with a combination of amlodipine besylate equivalent to 2.5 mg, 5 mg or 10 mg of amlodipine, with 10 mg, 20 mg or 40 mg of benazepril hydrochloride providing for the following available combinations: 2.5/10 mg, 5/10 mg, 5/20 mg, 5/40 mg, 10/20 mg and 10/40 mg.

The inactive ingredients of the capsules are calcium phosphate, cellulose compounds, colloidal silicon dioxide, crospovidone, gelatin, hydrogenated castor oil (not present in 5/40 mg or 10/40 mg strengths), iron oxides, lactose, magnesium stearate, polysorbate 80, silicon dioxide, sodium lauryl sulfate, sodium starch (potato) glycolate, starch (corn), talc, and titanium dioxide.

12 CLINICAL PHARMACOLOGY

12.1 Mechanism of Action

Benazepril

Benazepril and benazeprilat inhibit angiotensin-converting enzyme (ACE) in human subjects and in animals. ACE is a peptidyl dipeptidase that catalyzes the conversion of angiotensin I to the vasoconstrictor substance angiotensin II. Angiotensin II also stimulates aldosterone secretion by the adrenal cortex.

Inhibition of ACE results in decreased plasma angiotensin II, which leads to decreased vasopressor activity and to decreased aldosterone secretion. The latter decrease may result in a small increase of serum potassium. Hypertensive patients treated with benazepril and amlodipine for up to 56 weeks had elevations of serum potassium up to 0.2 mEq/L [see Warnings and Precautions (5)].

Removal of angiotensin II negative feedback on renin secretion leads to increased plasma renin activity. In animal studies, benazepril had no inhibitory effect on the vasopressor response to angiotensin II and did not interfere with the hemodynamic effects of the autonomic neurotransmitters acetylcholine, epinephrine, and norepinephrine.

ACE is identical to kininase, an enzyme that degrades bradykinin. Whether increased levels of bradykinin, a potent vasodepressor peptide, play a role in the therapeutic effects of Lotrel remains to be elucidated.

While the mechanism through which benazepril lowers blood pressure is believed to be primarily suppression of the renin-angiotensin aldosterone system, benazepril has an antihypertensive effect even in patients with low-renin hypertension.

Amlodipine

Amlodipine is a dihydropyridine calcium antagonist (calcium ion antagonist or slow channel blocker) that inhibits the transmembrane influx of calcium ions into vascular smooth muscle and cardiac muscle. Experimental data suggest that amlodipine binds to both dihydropyridine and nondihydropyridine binding sites. The contractile processes of cardiac muscle and vascular smooth muscle are dependent upon the movement of extracellular calcium ions into these cells through specific ion channels. Amlodipine inhibits calcium ion influx across cell membranes selectively, with a greater effect on vascular smooth muscle cells than on cardiac muscle cells. Negative inotropic effects can be detected in vitro but such effects have not been seen in intact animals at therapeutic doses. Serum calcium concentration is not affected by amlodipine. Within the physiologic pH range, amlodipine is an ionized compound (pKa=8.6), and its kinetic interaction with the calcium channel receptor is characterized by a gradual rate of association and dissociation with the receptor binding site, resulting in a gradual onset of effect.

Amlodipine is a peripheral arterial vasodilator that acts directly on vascular smooth muscle to cause a reduction in peripheral vascular resistance and reduction in blood pressure.

12.2 Pharmacodynamics

Benazepril

Single and multiple doses of 10 mg or more of benazepril cause inhibition of plasma ACE activity by at least 80%-90% for at least 24 hours after dosing. For up to 4 hours after a 10-mg dose, pressor responses to exogenous angiotensin I were inhibited by 60%-90%.

Administration of benazepril to patients with mild-to-moderate hypertension results in a reduction of both supine and standing blood pressure to about the same extent, with no compensatory tachycardia. Symptomatic postural hypotension is infrequent, although it can occur in patients who are salt and/or volume depleted [see Warnings and Precautions (5)].

The antihypertensive effects of benazepril were not appreciably different in patients receiving high- or low-sodium diets.

In normal human volunteers, single doses of benazepril caused an increase in renal blood flow but had no effect on glomerular filtration rate.

Amlodipine

Following administration of therapeutic doses to patients with hypertension, amlodipine produces vasodilation resulting in a reduction of supine and standing blood pressures. These decreases in blood pressure are not accompanied by a significant change in heart rate or plasma catecholamine levels with chronic dosing. Plasma concentrations correlate with effect in both young and elderly patients.

As with other calcium channel blockers, hemodynamic measurements of cardiac function at rest and during exercise (or pacing) in patients with normal ventricular function treated with amlodipine have generally demonstrated a small increase in cardiac index without significant influence on dP/dt or on left ventricular end diastolic pressure or volume. In hemodynamic studies, amlodipine has not been associated with a negative inotropic effect when administered in the therapeutic dose range to intact animals and humans, even when coadministered with beta blockers to humans.

Amlodipine does not change sinoatrial (SA) nodal function or atrioventricular (AV) conduction in intact animals or humans. In clinical studies in which amlodipine was administered in combination with beta blockers to patients with either hypertension or angina, no adverse effects on electrocardiographic parameters were observed.

12.3 Pharmacokinetics

The rate and extent of absorption of benazepril and amlodipine from Lotrel are not significantly different, respectively, from the rate and extent of absorption of benazepril and amlodipine from individual tablet formulations. Absorption from the individual tablets is not influenced by the presence of food in the gastrointestinal tract; food effects on absorption from Lotrel have not been studied.

Following oral administration of Lotrel, peak plasma concentrations of benazepril are reached in 0.5-2 hours. Cleavage of the ester group (primarily in the liver) converts benazepril to its active metabolite, benazeprilat, which reaches peak plasma concentrations in 1.5-4 hours. The extent of absorption of benazepril is at least 37%.

Peak plasma concentrations of amlodipine are reached 6-12 hours after administration of Lotrel; the extent of absorption is 64%-90%.

The apparent volumes of distribution of amlodipine and benazeprilat are about 21 L/kg and 0.7 L/kg, respectively. Approximately 93% of circulating amlodipine is bound to plasma proteins, and the bound fraction of benazeprilat is slightly higher. On the basis of in vitro studies, benazeprilat’s degree of protein binding should be unaffected by age, by hepatic dysfunction, or—over the therapeutic concentration range—by concentration.

Benazeprilat has much greater ACE-inhibitory activity than benazepril, and the metabolism of benazepril to benazeprilat is almost complete. Only trace amounts of an administered dose of benazepril can be recovered unchanged in the urine; about 20% of the dose is excreted as benazeprilat, 8% as benazeprilat glucuronide, and 4% as benazepril glucuronide.

Amlodipine is extensively metabolized in the liver, with 10% of the parent compound and 60% of the metabolites excreted in the urine. In patients with hepatic dysfunction, decreased clearance of amlodipine may increase the area-under-the-plasma-concentration curve by 40%-60%, and dosage reduction may be required [see Dosage and Administration (2)]. In patients with renal impairment, the pharmacokinetics of amlodipine are essentially unaffected.

Benazeprilat’s effective elimination half-life is 10-11 hours, while that of amlodipine is about 2 days, so steady-state levels of the two components are achieved after about a week of once-daily dosing. The clearance of benazeprilat from the plasma is primarily renal, but biliary excretion accounts for 11%-12% of benazepril elimination in normal subjects. In patients with severe renal insufficiency (creatinine clearance less than 30 mL/min), peak benazeprilat levels and the time to steady state may be increased [see Dosage and Administration (2)]. In patients with hepatic impairment, on the other hand, the pharmacokinetics of benazeprilat are essentially unaffected.

Although the pharmacokinetics of benazepril and benazeprilat are unaffected by age, clearance of amlodipine is decreased in the elderly, with resulting increases of 35%-70% in peak plasma levels, elimination half-life, and area-under-the-plasma-concentration curve. Dose adjustment may be required.

13 NONCLINICAL TOXICOLOGY

13.1 Carcinogenesis, Mutagenesis, Impairment of Fertility

Carcinogenicity and mutagenicity studies have not been conducted with this combination. However, these studies have been conducted with amlodipine and benazepril alone (see below). No adverse effects on fertility occurred when the benazepril:amlodipine combination was given orally to rats of either sex at doses up to 15:7.5 mg (benazepril:amlodipine)/kg/day, prior to mating and throughout gestation.

Benazepril

No evidence of carcinogenicity was found when benazepril was administered to rats and mice for up to two years at doses of up to 150 mg/kg/day. When compared on the basis of body surface area, this dose is 18 and 9 times (rats and mice, respectively) the maximum recommended human dose (calculations assume a patient weight of 60 kg). No mutagenic activity was detected in the Ames test in bacteria, in an in vitro test for forward mutations in cultured mammalian cells, or in a nucleus anomaly test. At doses of 50-500 mg/kg/day (6-60 times the maximum recommended human dose on a body surface area basis), benazepril had no adverse effect on the reproductive performance of male and female rats.

Amlodipine

Rats and mice treated with amlodipine maleate in the diet for up to two years, at concentrations calculated to provide daily dosage levels of 0.5, 1.25, and 2.5 mg amlodipine/kg/day, showed no evidence of a carcinogenic effect of the drug. For the mouse, the highest dose was, on a body surface area basis, similar to the maximum recommended human dose [MRHD] of 10 mg amlodipine/day. For the rat, the highest dose was, on a body surface area basis, about two and a half times the MRHD. (Calculations based on a 60 kg patient.) Mutagenicity studies conducted with amlodipine maleate revealed no drug-related effects at either the gene or chromosome level. There was no effect on the fertility of rats treated orally with amlodipine maleate (males for 64 days and females for 14 days prior to mating) at doses of up to 10 mg amlodipine/kg/day (about 10 times the MRHD of 10 mg/day on a body surface area basis).

13.3 Reproductive Toxicity

When rats received benazepril:amlodipine at doses ranging from 5:2.5 to 50:25 mg/kg/day, dystocia was observed at an increasing dose-related incidence at all doses tested. On a body surface area basis, the 2.5 mg/kg/day dose of amlodipine is 3.6 times the amlodipine dose delivered when the maximum recommended dose of Lotrel is given to a 50-kg woman. Similarly, the 5 mg/kg/day dose of benazepril is approximately twice the benazepril dose delivered when the maximum recommended dose of Lotrel is given to a 50-kg woman. No teratogenic effects were seen when benazepril and amlodipine were administered in combination to pregnant rats or rabbits. Rats received doses of up to 50:25 mg (benazepril:amlodipine)/kg/day (24 times the maximum recommended human dose on a body surface area basis, assuming a 50-kg woman). Rabbits received doses of up to 1.5:0.75 mg/kg/day (equivalent to the maximum recommended dose of Lotrel given to a 50-kg woman).

Benazepril

No teratogenic effects of benazepril were seen in studies of pregnant rats, mice, and rabbits. On a body surface area basis, the maximum doses used in these studies were 60 times (in rats), 9 times (in mice), and about equivalent to (in rabbits) the maximum recommended human dose (assuming a 50-kg woman).

Amlodipine

No evidence of teratogenicity or other embryo/fetal toxicity was found when pregnant rats and rabbits were treated orally with amlodipine maleate at doses of up to 10 mg amlodipine/kg/day (respectively, about 10 and 20 times the maximum recommended human dose [MRHD] of 10 mg amlodipine on a body surface area basis) during their respective periods of major organogenesis. (Calculations based on a patient weight of 60 kg.) However, litter size was significantly decreased (by about 50%) and the number of intrauterine deaths was significantly increased (about 5-fold) for rats receiving amlodipine maleate at a dose equivalent to 10 mg amlodipine/kg/day for 14 days before mating and throughout mating and gestation. Amlodipine maleate has been shown to prolong both the gestation period and the duration of labor in rats at this dose. There are no adequate and well-controlled studies in pregnant women. Amlodipine should be used during pregnancy only if the potential benefit justifies the potential risk to the fetus.

14 CLINICAL STUDIES

Over 950 patients received Lotrel once daily in six double-blind, placebo-controlled studies. The antihypertensive effect of a single dose persisted for 24 hours, with peak reductions achieved 2-8 hours after dosing.

Once-daily doses of benazepril/amlodipine using benazepril doses of 10-20 mg and amlodipine doses of 2.5-10 mg decreased seated pressure (systolic/diastolic) 24 hours after dosing by about 10-25/6-13 mmHg.

In two studies in patients not adequately controlled on either benazepril 40 mg alone (n=329) or amlodipine 10 mg alone (n=812) once daily doses of Lotrel 10/40 mg further decreased seated blood pressure compared to the respective monotherapy alone.

Combination therapy was effective in blacks and nonblacks. Both components contributed to the antihypertensive efficacy in nonblacks, but virtually all of the antihypertensive effect in blacks could be attributed to the amlodipine component. Among nonblack patients in placebo-controlled trials comparing Lotrel to the individual components, the blood pressure lowering effects of the combination were shown to be additive and in some cases synergistic.

During chronic therapy with Lotrel, the maximum reduction in blood pressure with any given dose is generally achieved after 1-2 weeks. The antihypertensive effects of Lotrel have continued during therapy for at least 1 year. Abrupt withdrawal of Lotrel has not been associated with a rapid increase in blood pressure.

16 HOW SUPPLIED/STORAGE AND HANDLING

Lotrel is available as capsules containing amlodipine besylate equivalent to 2.5 mg, 5 mg or 10 mg of amlodipine, with 10 mg, 20 mg or 40 mg of benazepril hydrochloride providing for the following available combinations: 2.5/10 mg, 5/10 mg, 5/20 mg, 5/40 mg, 10/20 mg and 10/40 mg. All six strengths are packaged in bottles of 100 capsules.

Capsules are imprinted with “Lotrel” and appropriate code.

Dose | Capsule Color/Code | Bottles of | NDC Code
2.5/10 mg | white with 2 gold bands/2255 | 10 | 54868-4066-1
 |  | 30 | 54868-4066-0
5/10 mg | light brown with 2 white bands/2260 | 10 | 54868-4073-1
 |  | 30 | 54868-4073-0
 |  | 60 | 54868-4073-2
 |  | 100 | 54868-4073-3
5/20 mg | pink with 2 white bands/2265 | 10 | 54868-4074-2
 |  | 30 | 54868-4074-0
 |  | 60 | 54868-4074-4
 |  | 90 | 54868-4074-1
 |  | 100 | 54868-4074-3
5/40 mg | light blue with 2 white bankds/0384 | 10 | 54868-5783-0
 |  | 30 | 54868-5783-1
10/20 mg | purple (amethyst) with 2 white bands/0364 | 10 | 54868-4870-1
 |  | 30 | 54868-4870-0
 |  | 90 | 54868-4870-2
10/40 mg | dark blue with 2 white bands/0379 | 10 | 54868-5690-0
 |  | 30 | 54868-5690-1
 |  | 90 | 54868-5690-3
 |  | 100 | 54868-5690-2

Storage: Store at 25°C (77°F); excursions permitted to 15-30°C (59-86°F). [See USP controlled room temperature.] Protect from moisture. Dispense in tight container (USP).

17 PATIENT COUNSELING INFORMATION

Information for Patients

Female patients of childbearing age should be told about the consequences of exposure to Lotrel during pregnancy. Discuss treatment options with women planning to become pregnant. Patients should be asked to report pregnancies to their physicians as soon as possible.

FDA-Approved Patient Labeling

LOTREL®‚ (low-TREL)

amlodipine besylate/benazepril hydrochloride capsules

Read this Patient Information leaflet before you start taking LOTREL and each time you get a refill. There may be new information. This leaflet does not replace talking with your doctor. If you have any questions, ask your doctor or pharmacist.

What is the most important information I should know about LOTREL?

- LOTREL can cause harm or death to an unborn baby.
- Talk to your doctor about other ways to lower your blood pressure if you plan to become pregnant.
- If you get pregnant while taking LOTREL, tell your doctor right away.

What is LOTREL?

LOTREL contains two prescription medicines that work together to lower blood pressure: amlodipine besylate (the active ingredient found in Norvasc®), a calcium channel blocker, and benazepril hydrochloride (Lotensin®), an ACE inhibitor. Your doctor will prescribe LOTREL only after other medicines haven’t worked.

High Blood Pressure (hypertension). Blood pressure is the force of blood in your blood vessels. You have high blood pressure when the force is too much. LOTREL can help your blood vessels relax so your blood pressure is lower.

LOTREL has not been studied in children.

Who should not take LOTREL?

Don’t take LOTREL if you are allergic to any of the ingredients. There is a complete list at the end of this leaflet.

What should I tell my Doctor before taking LOTREL?

Tell your doctor about all your medical conditions, including if:

- you are pregnant or plan to become pregnant. See “What is the most important information I should know about LOTREL?”
- you are breastfeeding. LOTREL may pass into your milk. Don’t breastfeed while you are taking LOTREL.
- you have a heart condition
- you have liver problems
- you have kidney problems
- you have diabetes (high blood sugar)
- you have systemic lupus erythematosus (SLE), scleroderma or a collagen vascular disease. Ask your doctor if you are not sure.

Keep a list of your medicines with you, including vitamins and natural or herbal remedies, to show your doctor or pharmacist. Some of your other medicines and LOTREL could affect each other, causing serious side effects. Tell your doctor about all your medicines, especially:

- medicines for high blood pressure or heart failure
- water pills, extra potassium or a salt substitute
- Lithium (Eskalith®, Lithobid®)

How do I take LOTREL?

- Take LOTREL exactly as your doctor tells you.
- Take LOTREL at the same time each day, with or without food.
- If you miss a dose, take it as soon as you remember. If it is more than 12 hours, just take your next dose at the regular time.
- Your doctor may test for kidney problems or check your blood potassium level.
- If you take too much LOTREL, call your doctor or Poison Control Center, or go to the emergency room.
- Tell all your doctors or dentist you are taking LOTREL if you:
  - are going to have surgery
  - are getting allergy shots for bee stings
  - go for kidney dialysis

What are the possible side effects of LOTREL?

LOTREL can cause serious side effects including:

- serious allergic reactions that can be life threatening.
  Stop LOTREL and get emergency help right away if you get:
  - swelling of your face, eyelids, lips, tongue or throat
  - have trouble swallowing
  - asthma (wheezing) or other breathing problems
  These allergic reactions are rare but happen more times in people who are African-American.

- low blood pressure (hypotension). Low blood pressure is most likely to happen if you also take water pills, are on a low salt diet, get dialysis treatments, have heart problems or get sick with vomiting or diarrhea. Lie down if you feel faint or dizzy.
- liver problems. Call your doctor if:
- you have nausea
- you feel more tired or weaker than usual
- you have itching
- your skin or eyes look yellow
- you have pain in your upper right stomach
- you have flu-like symptoms
- low white blood cells. Low white blood cells happen more in people who have kidney problems and collagen vascular diseases. Low white blood cells can give you a higher chance for getting infections. Call your doctor if you get a fever, sore throat, or other signs of infection that do not go away.
- kidney problems. Kidney problems may get worse in people that already have kidney disease. Some people will have changes on blood tests for kidney function and need a lower dose of LOTREL. Call your doctor if you get swelling in your feet, ankles, or hands or unexplained weight gain.
- more chest pain and heart attacks in people that already have severe heart problems. Get emergency help if you get worse chest pain or chest pain that does not go away.

The more common side effects of LOTREL are:

- Cough
- Dizziness
- Headache
- Swelling of the feet, ankles, and hands

These are not all the side effects of LOTREL. For a complete list, ask your doctor or pharmacist.

How do I store LOTREL?

- Store LOTREL at room temperature (59-86°F).
- Keep LOTREL in a closed container in a dry place.
- Keep LOTREL and all medicines out of the reach of children.

General Information about LOTREL

Doctors can also use medicine for a condition that is not in the patient information leaflet. Take LOTREL the way your doctor tells you. Do not share it with other people. It may harm them.

For more information, ask your doctor or pharmacist, visit www.LOTREL.com on the Internet, or call 1-888-669-6682.

What are the ingredients in LOTREL?

Active ingredients: amlodipine besylate (the active ingredient found in Norvasc®), benazepril hydrochloride (Lotensin®)

Inactive ingredients: calcium phosphate, cellulose compounds, colloidal silicon dioxide, crospovidone, gelatin, hydrogenated castor oil (not present in 5/40 mg and 10/40 mg strengths), iron oxides, lactose, magnesium stearate, polysorbate 80, silicon dioxide, sodium lauryl sulfate, sodium starch (potato) glycolate, starch (corn), talc, and titanium dioxide.

Norvasc® is a registered trademark of Pfizer, Inc. Lotensin® is a registered trademark of Novartis Corp. Eskalith® and Lithobid® are registered trademarks of Noven Therapeutics, LLC.

Distributed by:
Novartis Pharmaceuticals Corporation
East Hanover, New Jersey 07936

© Novartis

T2012-43/T2012-44
January 2012/January 2012

Relabeling and Repackaging by:
Physicians Total Care, Inc.
Tulsa, Oklahoma 74146

PACKAGE LABEL

PRINCIPAL DISPLAY PANEL

Package Label – 2.5 / 10 mg

Rx Only

Lotrel®

amlodipine besylate

(equivalient to amlodipine 2.5 mg)

benazepril HCL 10 mg

PACKAGE LABEL

PRINCIPAL DISPLAY PANEL

Package Label – 5/ 10 mg

Rx Only

Lotrel®

amlodipine besylate

(equivalient to amlodipine 5 mg)

benazepril HCL 10 mg

PACKAGE LABEL

PRINCIPAL DISPLAY PANEL

Package Label – 5/ 20 mg

Rx Only

Lotrel®

amlodipine besylate

(equivalient to amlodipine 5 mg)

benazepril HCL 20 mg

PACKAGE LABEL

PRINCIPAL DISPLAY PANEL

Package Label – 5/ 40 mg

Rx Only

Lotrel®

amlodipine besylate

(equivalient to amlodipine 5 mg)

benazepril HCL 40 mg

PACKAGE LABEL

PRINCIPAL DISPLAY PANEL

Package Label – 10 / 20 mg

Rx Only

Lotrel®

amlodipine besylate

(equivalient to amlodipine10 mg)

benazepril HCL 20 mg

PACKAGE LABEL

PRINCIPAL DISPLAY PANEL

Package Label – 10 / 40 mg

Rx Only

Lotrel®

amlodipine besylate

(equivalient to amlodipine10 mg)

benazepril HCL 40 mg